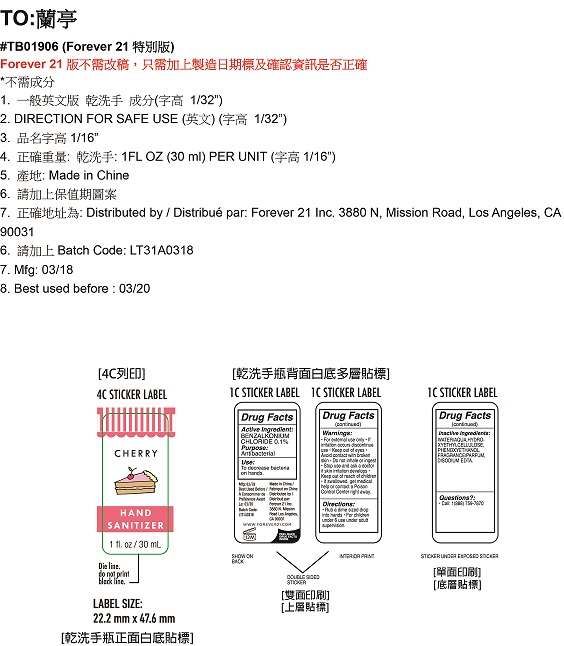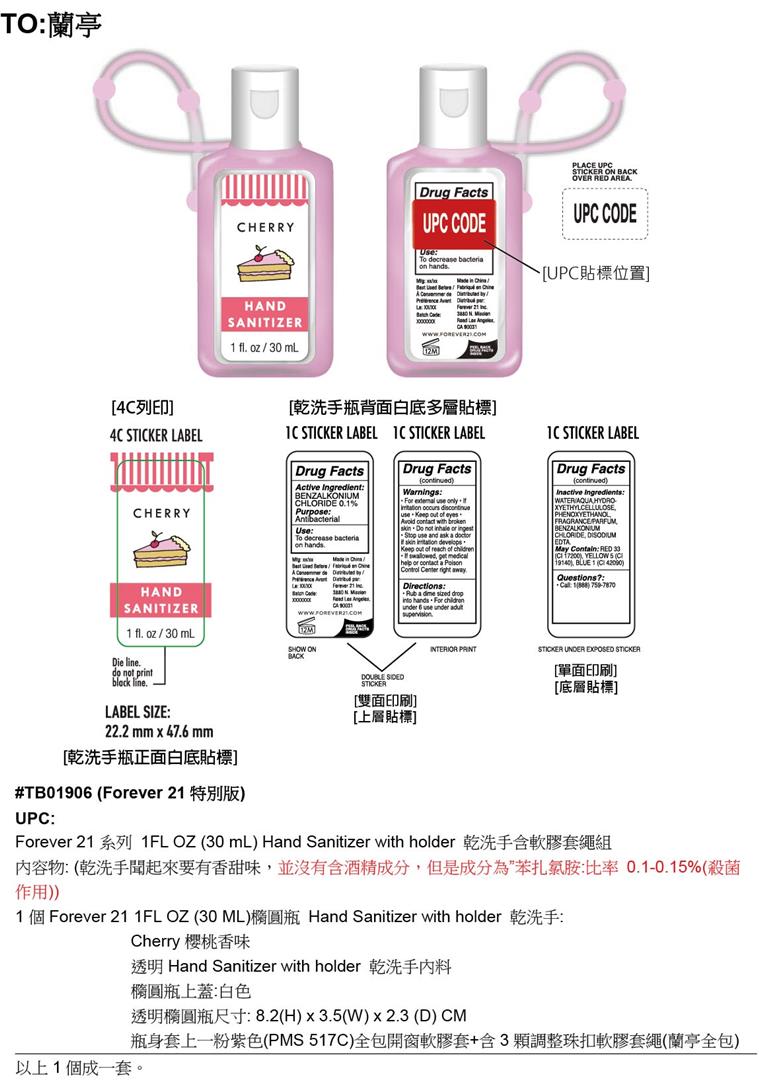 DRUG LABEL: Cherry Hand Sanitizer
NDC: 54860-090 | Form: GEL
Manufacturer: Shenzhen Lantern Science Co., Ltd.
Category: otc | Type: HUMAN OTC DRUG LABEL
Date: 20180206

ACTIVE INGREDIENTS: BENZALKONIUM CHLORIDE 0.1 g/100 mL
INACTIVE INGREDIENTS: HYDROXYETHYL ETHYLCELLULOSE; EDETATE DISODIUM; PHENOXYETHANOL; WATER

Cherry Hand Sanitizer

Active Ingredient

Benzalkonium Chloride 0.1%

PURPOSE

Antibacterial

Keep out of reach of children.

Warnings

- for external use only
- if irritation occurs discontinue use
- keep out of eyes
- avoid contact with broken skin
- do not inhale or ingest
- stop use and ask if doctor if skin irritation develops
- keep out of reach of children
- if swallowed, get medical help or contact a poison control center right away.

Directions

- Rub a dime sized drop into hands.
- For children under 6 use under adult supervision.

Inactive Ingredients

water/aqua, hydroxyethylcellulose, phenoxyethanol, fragrance/parfum, disodium edta

INDICATIONS AND USAGE

To decrease bacteria on hands